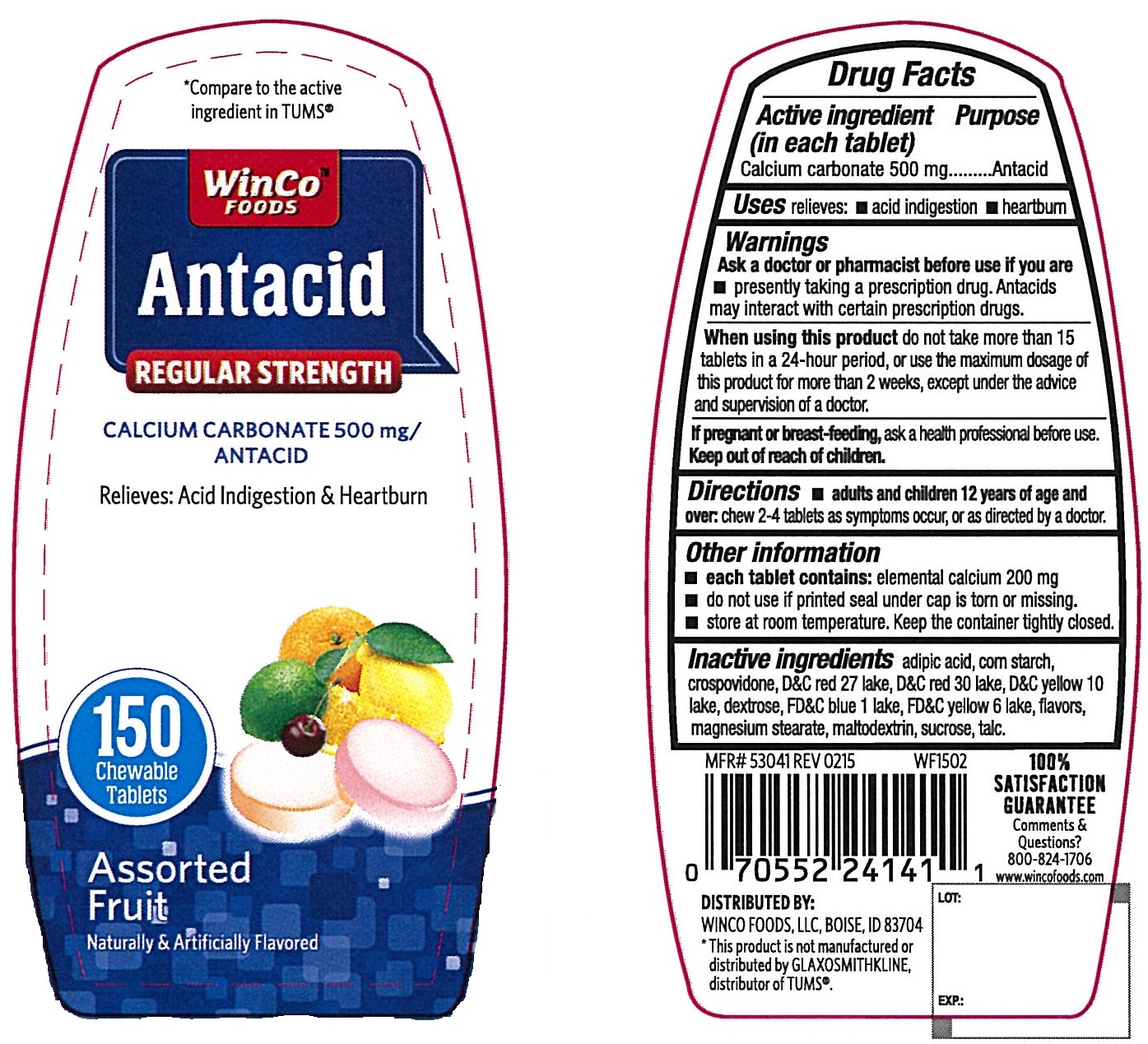 DRUG LABEL: Antacid
NDC: 67091-224 | Form: TABLET, CHEWABLE
Manufacturer: WinCo Foods, LLC
Category: otc | Type: HUMAN OTC DRUG LABEL
Date: 20220113

ACTIVE INGREDIENTS: CALCIUM CARBONATE 500 mg/1 1
INACTIVE INGREDIENTS: ADIPIC ACID; STARCH, CORN; CROSPOVIDONE; D&C RED NO. 27; D&C RED NO. 30; D&C YELLOW NO. 10; DEXTROSE, UNSPECIFIED FORM; FD&C BLUE NO. 1; FD&C YELLOW NO. 6; MAGNESIUM STEARATE; MALTODEXTRIN; SUCROSE; TALC

Antacid Regular Strength Assorted Fruit

Active ingredient (in each tablet)

Calcium carbonate 500 mg

Purpose

Antacid

Uses

relieves

- acid indigestion
- heartburn

Warnings

Ask a doctor or pharmacist before use if you are

- presently taking a prescription drug. Antacids may interact with certain prescriptiom drugs.

When using this product

do not take more than 15 tablets in a 24-hour period, or use the maximum dosage of this product for more than 2 weeks, except under the advice and supervision of a doctor.

Directions

- chew 2-4 tablets as symptoms occur, or as directed by a doctor

Other information

- each tablet contains: elemental calcium 200 mg
- do not use if seal under cap is torn or missing
- store at room temperature. keep the container tightly closed.

Inactive ingredients

adipic acid, corn starch, crospovidone, D&C red 27 lake, D&C red 30 lake, D&C Yellow 10 lake, dextrose, FD&C blue 1 lake, FD&C yellow 6 lake, flavors, magnesium stearate, maltodextrin, sucrose, talc

Principal Display Panel

*Compare to the Active Ingredient in Tums®

WinCo Foods

Antacid

Regular Strength

CALCIUM CARBONATE 500 mg/ANTACID

Relieves: Acid Indigestion & Heartburn

Assorted Fruit

Naturally and Artificially Flavored

150 chewable tablets